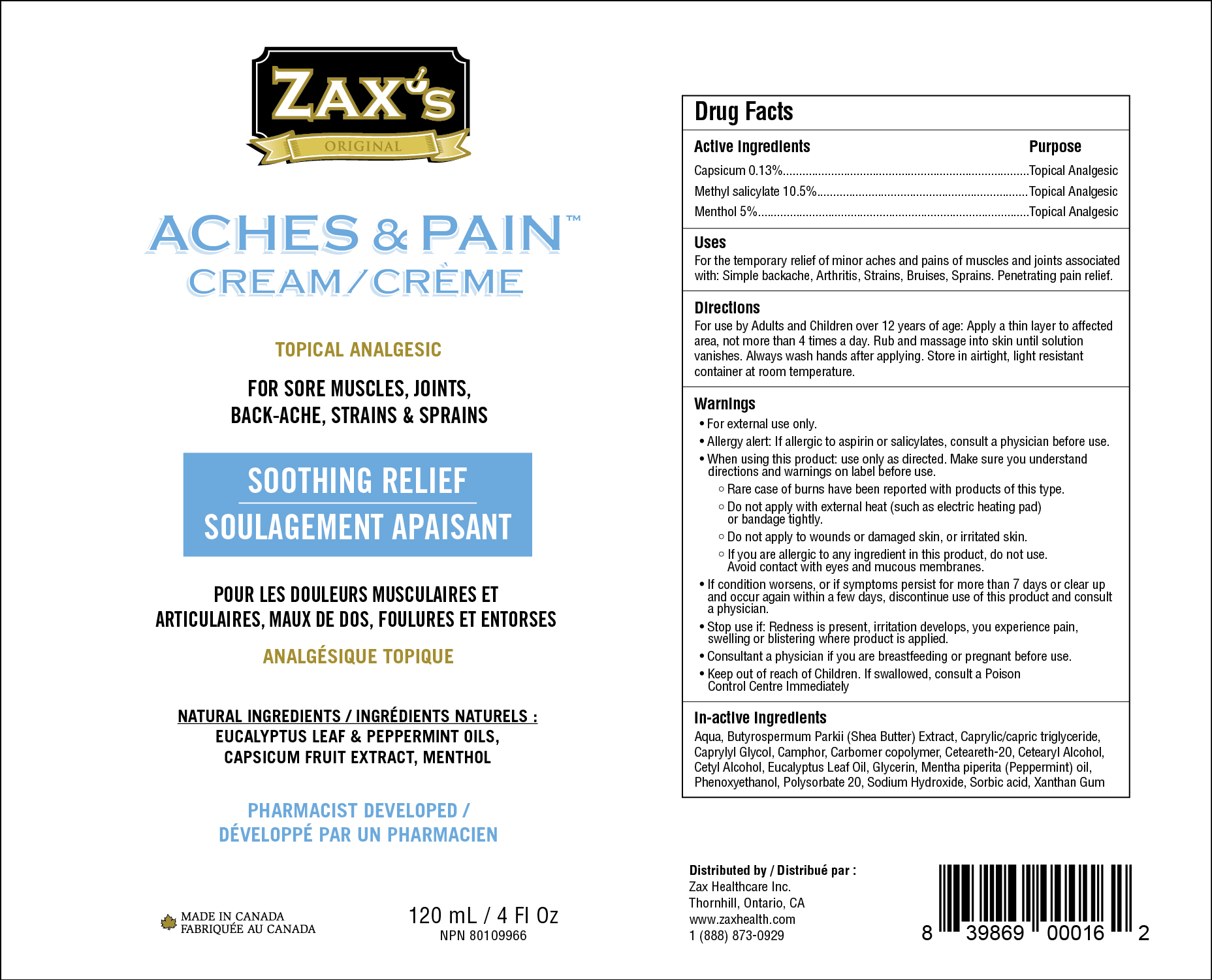 DRUG LABEL: Zaxs Aches and Pain
NDC: 82186-162 | Form: CREAM
Manufacturer: Zax Healthcare Inc.
Category: otc | Type: HUMAN OTC DRUG LABEL
Date: 20241212

ACTIVE INGREDIENTS: CAPSICUM 1.3 mg/1 g; MENTHOL 50 mg/1 g; METHYL SALICYLATE 105 mg/1 g
INACTIVE INGREDIENTS: CAPRYLYL GLYCOL; GLYCERIN; WATER; CAMPHOR (NATURAL); CARBOMER COPOLYMER TYPE A; EUCALYPTUS OIL; PEPPERMINT OIL; CAPRYLIC/CAPRIC/LAURIC TRIGLYCERIDE; POLYOXYL 20 CETOSTEARYL ETHER; BUTYROSPERMUM PARKII (SHEA) BUTTER UNSAPONIFIABLES; CETOSTEARYL ALCOHOL; CETYL ALCOHOL; PHENOXYETHANOL; SODIUM HYDROXIDE; SORBIC ACID; XANTHAN GUM; POLYSORBATE 20

Zax's Aches & Pain Cream/Creme

ACTIVE INGREDIENT

Capsicum 0.13%

Methyl Salicylate 10.5%

Menthol 5%

PURPOSE

Topical Analgesic

INDICATIONS AND USAGE

For the temporary relief of minor aches and pains of muscles and joints associated with: Simple backache, Arthritis, Strains, Bruises, Sprains. Penetrating pain relief.

DOSAGE AND ADMINISTRATION

For use by Adults and Children over 12 years of age: Apply a thin layer to affected area, not more than 4 times a day. Rub and massage into skin until solution vanishes. Always wash hands after applying. Store in airtight, light resistant container at room temperature.

WARNINGS

• For external use only.

•Allergy alert: If allergic to aspirin or salicylates, consult a physician before use.

•When using this product, use only as directed. Make sure you understand directions and warnings on label before use.

°Rare case of burns have been reported with products of this type.

°Do not apply with external heat (such as electric heating pad) or bandage tightly.

°Do not apply to wounds or damaged skin, or irritated skin.

°If you are allergic to any ingredient in this product, do not use. Avoid contact with eyes and mucous membranes.

•If condition worsens, or if symptoms persist for more than 7 days or clear up and occur again within a few days, discontinue use of this product and consult a physician.

•Stop use if: Redness is present, irritation develops, you experience pain, swelling or blistering where product is applied.

•Consult a physician if you are breastfeeding or pregnant before use.

Keep out of reach of children. If swallowed, consult a Poison Control Centre immediately.

INACTIVE INGREDIENT

Aqua, Butyrospermum Parkii (Shea Butter) Extraxt, Caprylic/capric triglyceride, Caprylyl Glycol, Camphor, Carbomer copolymer, Ceteareth-20, Cetearyl Alcohol, Cetyl Alcohol, Eucalyptus Leaf Oil, Glycerin, Mentha piperita (Peppermint) oil, Phenoxyethanol, Polysorbate 20, Sodium Hydroxide, Sorbic acid, Xanthan Gum

Tube Label